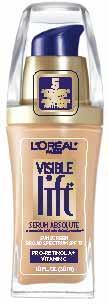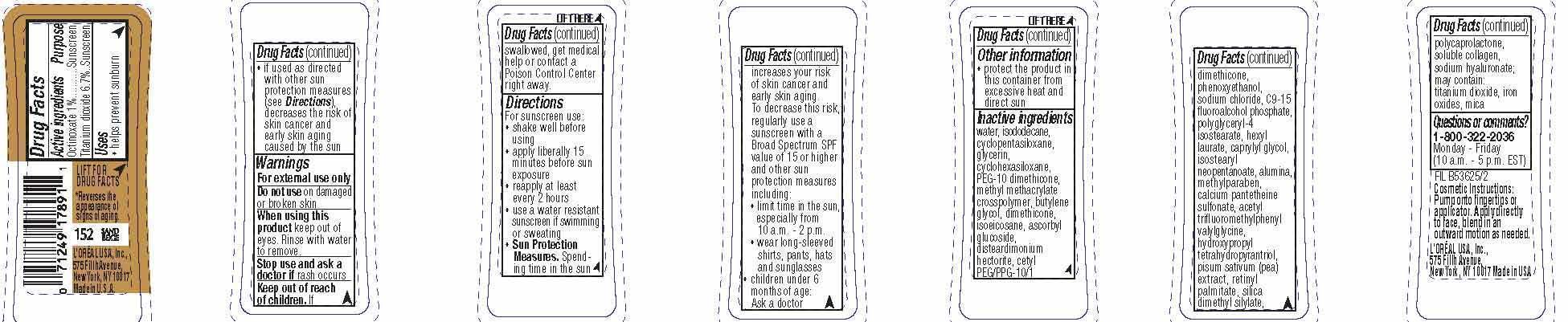 DRUG LABEL: LOreal Paris Visible lift Serum Absolute Advanced Age Reversing Makeup Broad Spectrum SPF 17
NDC: 49967-893 | Form: LIQUID
Manufacturer: L'Oreal USA Products Inc
Category: otc | Type: HUMAN OTC DRUG LABEL
Date: 20231229

ACTIVE INGREDIENTS: OCTINOXATE 10 mg/1 mL; TITANIUM DIOXIDE 67 mg/1 mL
INACTIVE INGREDIENTS: WATER; GLYCERIN; DIMETHICONE

Drug Facts

Active ingredients

Octinoxate 1%

Titanium dioxide 6.7%

Purpose

Sunscreen

Uses

- helps prevent sunburn

- if used as directed with other sun protection measures (see Directions), decreases the risk of skin cancer and early skin aging caused by the sun

Warnings

For external use only

Do not use

on damaged or broken skin

When using this product

keep out of eyes. Rinse with water to remove.

Stop use and ask a doctor if

rash occurs

Keep out of reach of children.

If swallowed, get medical help or contact a Poison Control Center right away.

Directions

For sunscreen use:

● shake well before using

● apply liberally 15 minutes before sun exposure

● reapply at least every 2 hours

● use a water resistant sunscreen if swimming or sweating

● Sun Protection Measures. Spending time in the sun increases your risk of skin cancer and early skin aging. To decrease this risk, regularly use a sunscreen with a Broad Spectrum SPF value of 15 or higher and other sun protection measures including:

● limit time in the sun, especially from 10 a.m. – 2 p.m.

● wear long-sleeved shirts, pants, hats, and sunglasses

● children under 6 months of age: Ask a doctor

Other information

protect the product in this container from excessive heat and direct sun

Inactive ingredients

water, isododecane, cyclopentasiloxane, glycerin, cyclohexasiloxane, PEG-10 dimethicone, methyl methacrylate crosspolymer, butylene glycol, dimethicone, isoeicosane, ascorbyl glucoside, disteardimonium hectorite, cetyl PEG/PPG-10/1 dimethicone, phenoxyethanol, sodium chloride, C9-15 fluoroalcohol phosphate, polyglyceryl-4 isostearate, hexyl laurate, caprylyl glycol, isostearyl neopentanoate, alumina, methylparaben, calcium pantetheine sulfonate, acetyl trifluoromethylphenyl valyglycine, hydroxypropyl tetrahydropyrantriol, pisum sativum (pea) extract, retinyl palmitate, silica dimethyl silylate, polycaprolactone, soluble collagen, sodium hyaluronate; may contain: titanium dioxide, iron oxides, mica

Questions or comments?

1-800-322-2036

Monday - Friday

(10 a.m. - 5 p.m. EST)